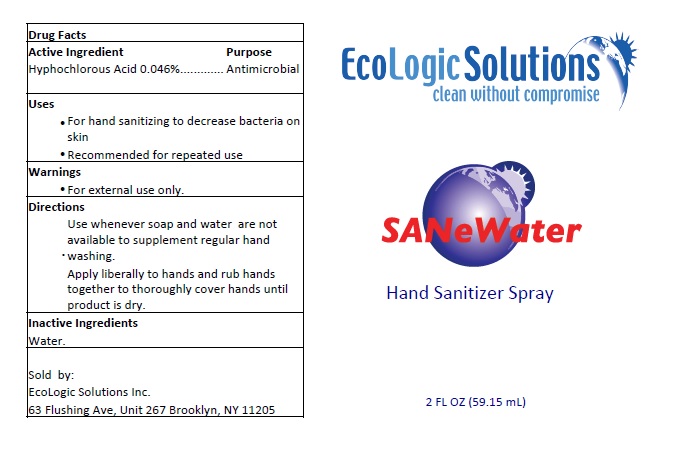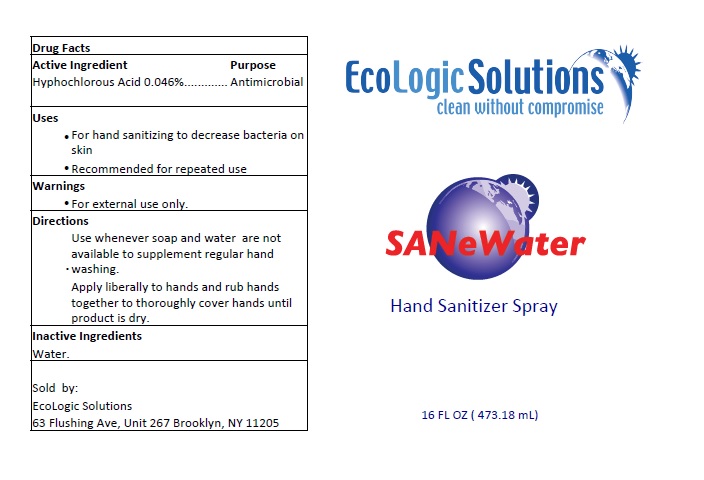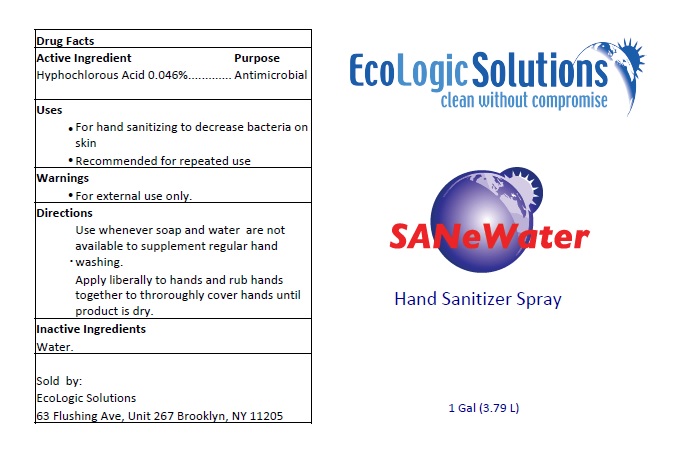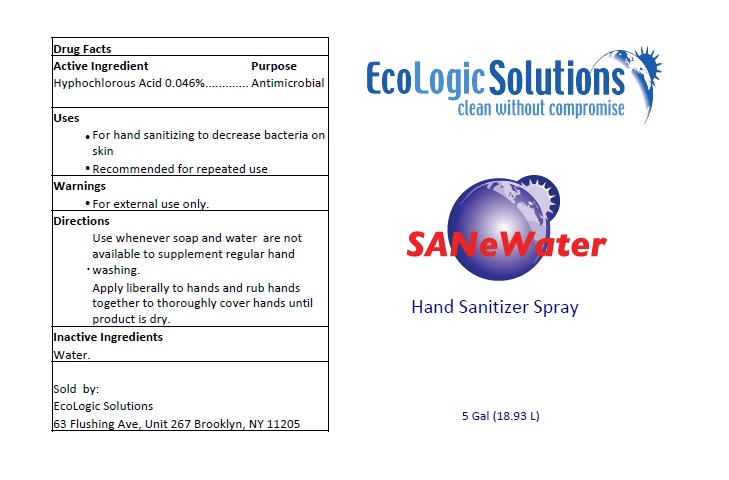 DRUG LABEL: SANe Water
NDC: 73747-001 | Form: LIQUID
Manufacturer: ECOLOGIC SOLUTIONS INC.
Category: otc | Type: HUMAN OTC DRUG LABEL
Date: 20200321

ACTIVE INGREDIENTS: HYPOCHLOROUS ACID 0.46 mg/1 mL
INACTIVE INGREDIENTS: WATER

SANe Water

Active Ingredient Purpose

Hypochlorous Acid 0.046% Antimicrobial

Uses

For hand sanitizing to decrease bacteria on skin.

Recommended for repeated use.

Warning

For external use only

Directions

- Use whenever soap and water are not available to supplement regular hand washing.

- Apply liberally to hands and rub hands together to thoroughly cover hands until product is dry.

Inactive Ingredient

Water